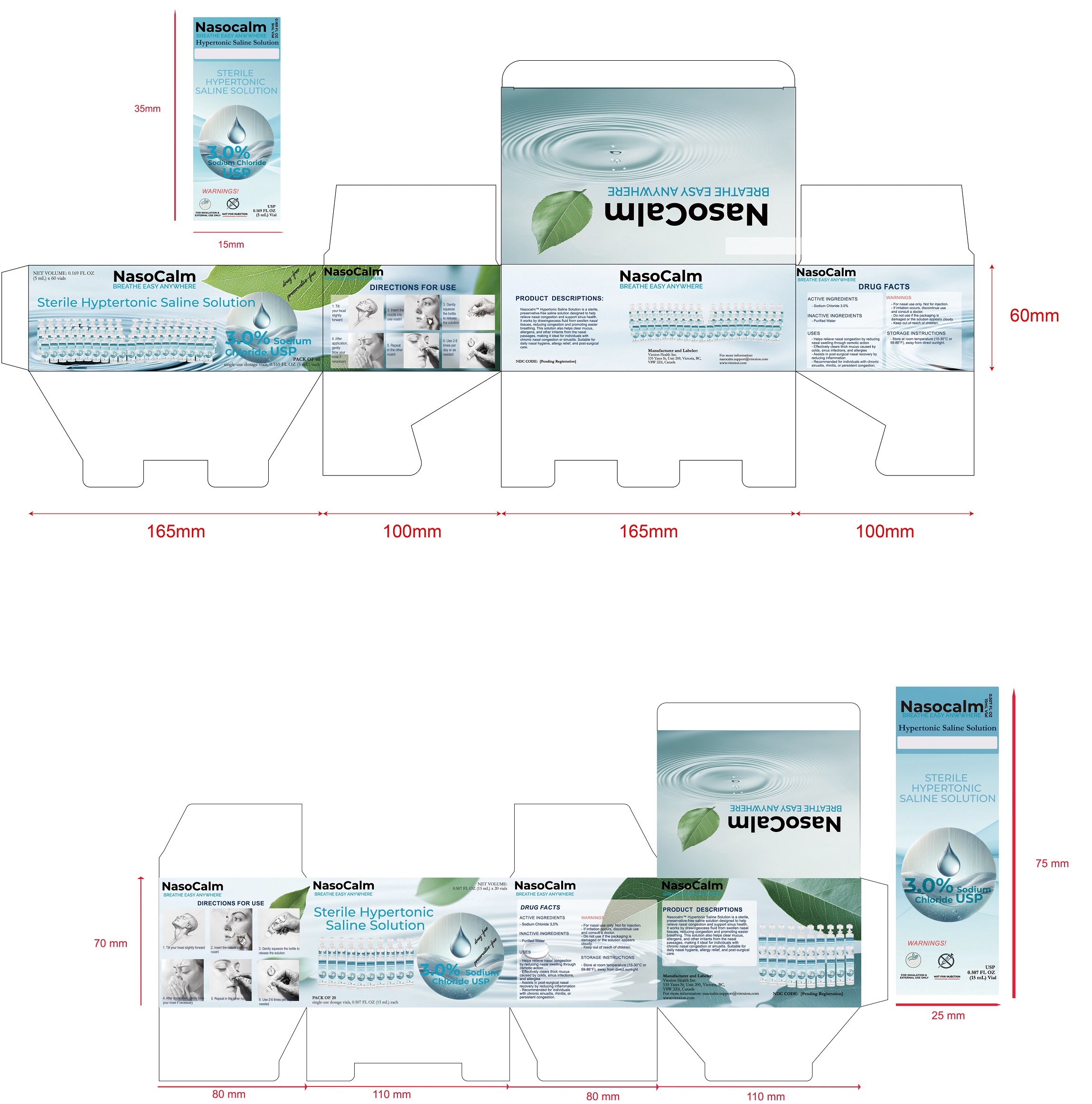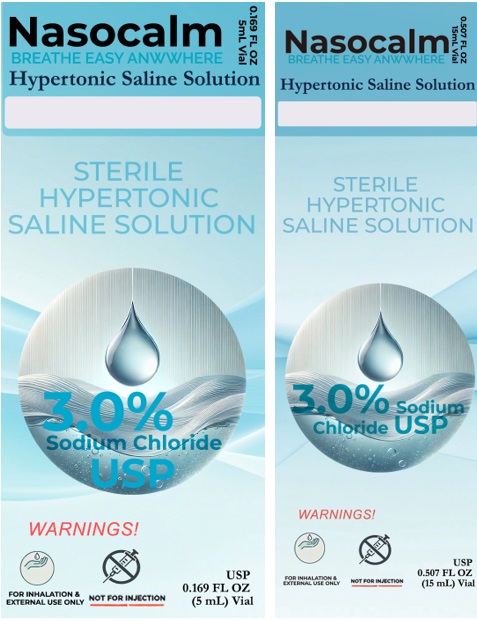 DRUG LABEL: Nasocalm
NDC: 85436-004 | Form: SOLUTION
Manufacturer: Virexion Health Inc.
Category: otc | Type: HUMAN OTC DRUG LABEL
Date: 20250328

ACTIVE INGREDIENTS: SODIUM CHLORIDE 3 mg/100 mg
INACTIVE INGREDIENTS: WATER

ACTIVE INGREDIENT

Sodium Chloride (NaCl) 3.0%

PURPOSE

Reduces nasal congestion, clears mucus and allergens, and assists in relieving symptoms of chronic nasal congestion or sinusitis by drawing out excess fluid from swollen nasal tissues.

INDICATIONS AND USAGE

Helps relieve nasal congestion by reducing nasal swelling through osmotic action
Effectively clears thick mucus caused by colds, sinus infections, and allergies
Assists in post-surgical nasal recovery by reducing inflammation
Recommended for individuals with chronic sinusitis, rhinitis, or persistent congestion.

WARNINGS

For nasal use only. Not for injections.

Do not use if the packaging is damaged or the solution appears cloudy.

Stop use and consult a doctor if irritation or infection occurs.

Keep out of reach of children.

Directions
1. Tilt your head slightly forward

2. Insert the nozzle into one nostril

3. Gently squeeze the bottle to release the solution

4. After application, gently blow your nose if necessary

5. Repeat in the other nostril

6. Use 2-6 times per day or as needed

7. Children and infants must be used under adult supervision. For children under 5 years old, please follow the advice of a healthcare professional

STORAGE AND HANDLING

1. Store at room temperature (15-30°C or 59-86°F).

2. Protect from extreme heat and direct sunlight.

INACTIVE INGREDIENT

Purified water USP